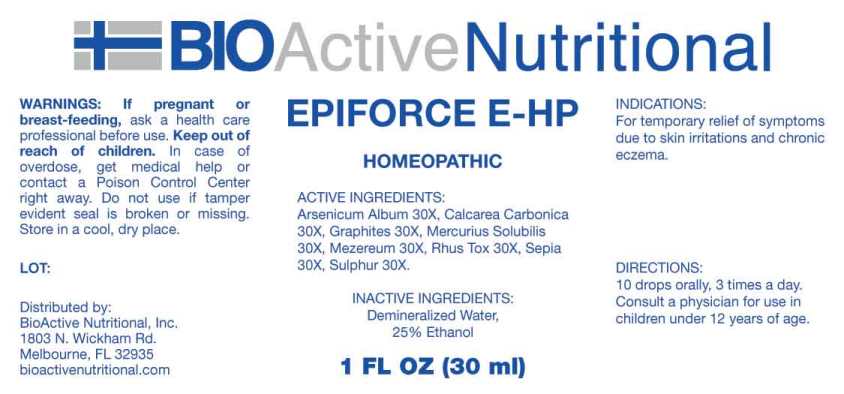 DRUG LABEL: Epiforce E-HP
NDC: 43857-0584 | Form: LIQUID
Manufacturer: BioActive Nutritional, Inc.
Category: homeopathic | Type: HUMAN OTC DRUG LABEL
Date: 20241017

ACTIVE INGREDIENTS: ARSENIC TRIOXIDE 30 [hp_X]/1 mL; OYSTER SHELL CALCIUM CARBONATE, CRUDE 30 [hp_X]/1 mL; GRAPHITE 30 [hp_X]/1 mL; MERCURIUS SOLUBILIS 30 [hp_X]/1 mL; DAPHNE MEZEREUM BARK 30 [hp_X]/1 mL; TOXICODENDRON PUBESCENS LEAF 30 [hp_X]/1 mL; SEPIA OFFICINALIS JUICE 30 [hp_X]/1 mL; SULFUR 30 [hp_X]/1 mL
INACTIVE INGREDIENTS: WATER; ALCOHOL

DRUG FACTS:

ACTIVE INGREDIENTS:

Arsenicum Album 30x, Calcarea Carbonica 30x, Graphites 30x, Mercurius Solubilis 30x, Mezereum 30x, Rhus Tox 30x, Sepia 30x, Sulphur 30x.

INDICATIONS:

For temporary relief of symptoms due to skin irritations and chronic eczema.

WARNINGS:

If pregnant or breast-feeding, ask a health care professional before use.

Keep out of reach of children. In case of overdose, get medical help or contact a Poison Control Center right away.

Do not use if tamper evident seal is broken or missing.

Store in a cool, dry place.

Keep out of reach of children. In case of overdose, get medical help or contact a Poison Control Center right away.

DIRECTIONS:

10 drops orally, 3 times a day. Consult a physician for use in children under 12 years of age.

INDICATIONS:

For temporary relief of symptoms due to skin irritations and chronic eczema.

INACTIVE INGREDIENTS:

Demineralized Water, 25% Ethanol

QUESTIONS:

Distributed by:
BioActive Nutritional, Inc.
1803 N. Wickham Rd.
Melbourne, FL 32935
bioactivenutritional.com

PACKAGE LABEL DISPLAY:

BIOActive Nutritional

EPIFORCE E-HP

HOMEOPATHIC

1 FL OZ (30 ml)